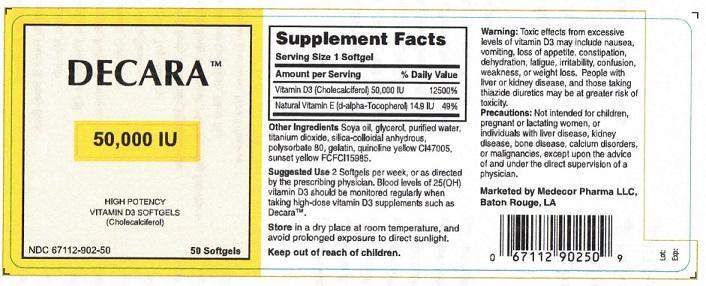 DRUG LABEL: DECARA HIGH POTENCY VITAMIN D3
NDC: 67112-902 | Form: CAPSULE
Manufacturer: Medecor Pharma, LLC
Category: other | Type: Dietary Supplement
Date: 20221227

ACTIVE INGREDIENTS: CHOLECALCIFEROL 50000 [iU]/1 1
INACTIVE INGREDIENTS: SOYBEAN OIL; GLYCERIN; WATER; TITANIUM DIOXIDE; SILICON DIOXIDE; POLYSORBATE 80; GELATIN; D&C YELLOW NO. 10; FD&C YELLOW NO. 6

MEDECOR PHARMA - DECARA HIGH POTENCY VITAMIN D3 (671120902)

STATEMENT OF IDENTITY

VITAMIN D3 (CHOLECALCIFEROL) 25,000 IU